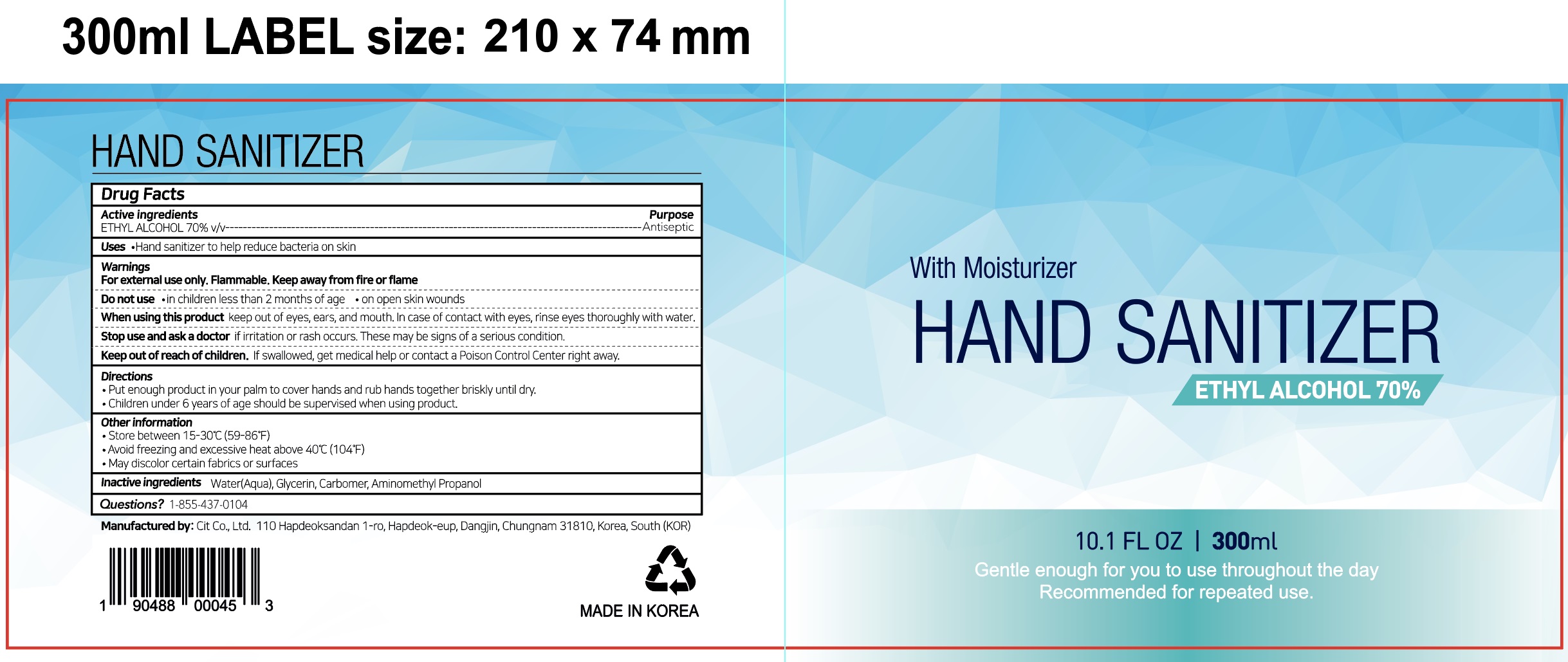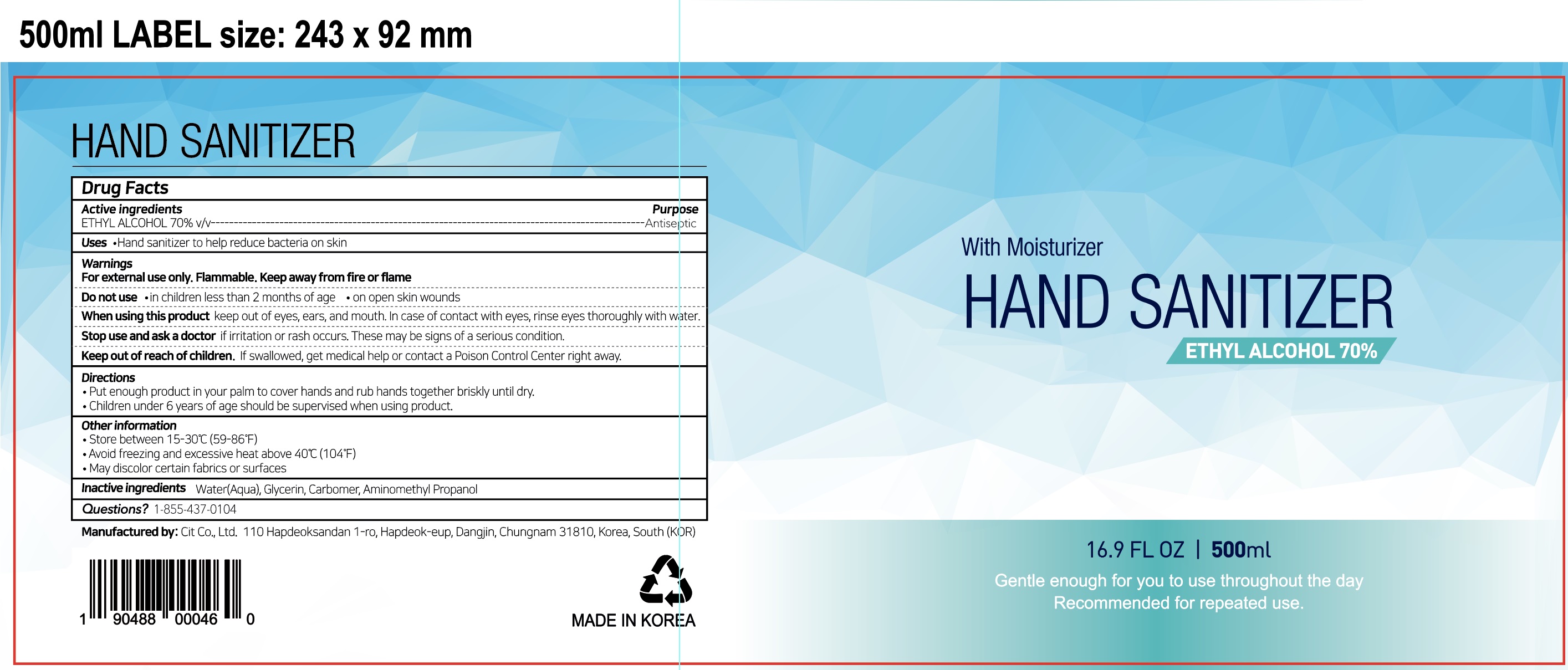 DRUG LABEL: HAND SANITIZER
NDC: 69133-110 | Form: GEL
Manufacturer: Cit Co., Ltd.
Category: otc | Type: HUMAN OTC DRUG LABEL
Date: 20220216

ACTIVE INGREDIENTS: ALCOHOL 70 mL/100 mL
INACTIVE INGREDIENTS: WATER; GLYCERIN; CARBOMER HOMOPOLYMER, UNSPECIFIED TYPE; AMINOMETHYLPROPANOL

HAND SANITIZER

ACTIVE INGREDIENT

ETHYL ALCOHOL 70% v/v

INACTIVE INGREDIENTS

Water(Aqua), Glycerin, Carbomer, Aminomethyl Propanol

PURPOSE

Antiseptic

WARNINGS

For external use only. Flammable. Keep away from fire or flame

--------------------------------------------------------------------------------------------------------
Do not use
• in children less than 2 months of age
• on open skin wounds
--------------------------------------------------------------------------------------------------------
When using this product keep out of eyes, ears, and mouth. In case of contact with eyes, rinse eyes thoroughly with water.
--------------------------------------------------------------------------------------------------------
Stop use and ask a doctor if irritation or rash occurs. These may be signs of a serious condition.

KEEP OUT OF REACH OF CHILDREN

If swallowed, get medical help or contact a Poison Control Center right away.

Uses

Hand sanitizer to help reduce bacteria on skin

Directions

• Put enough product in your palm to cover hands and rub hands together briskly until dry.
• Children under 6 years of age should be supervised when using product.

QUESTIONS?

+1-855-437-0104

Other information

• Store between 15-30C (59-86F)
• Avoid freezing and excessive heat above 40C (104F)
• May discolor certain fabrics or surfaces